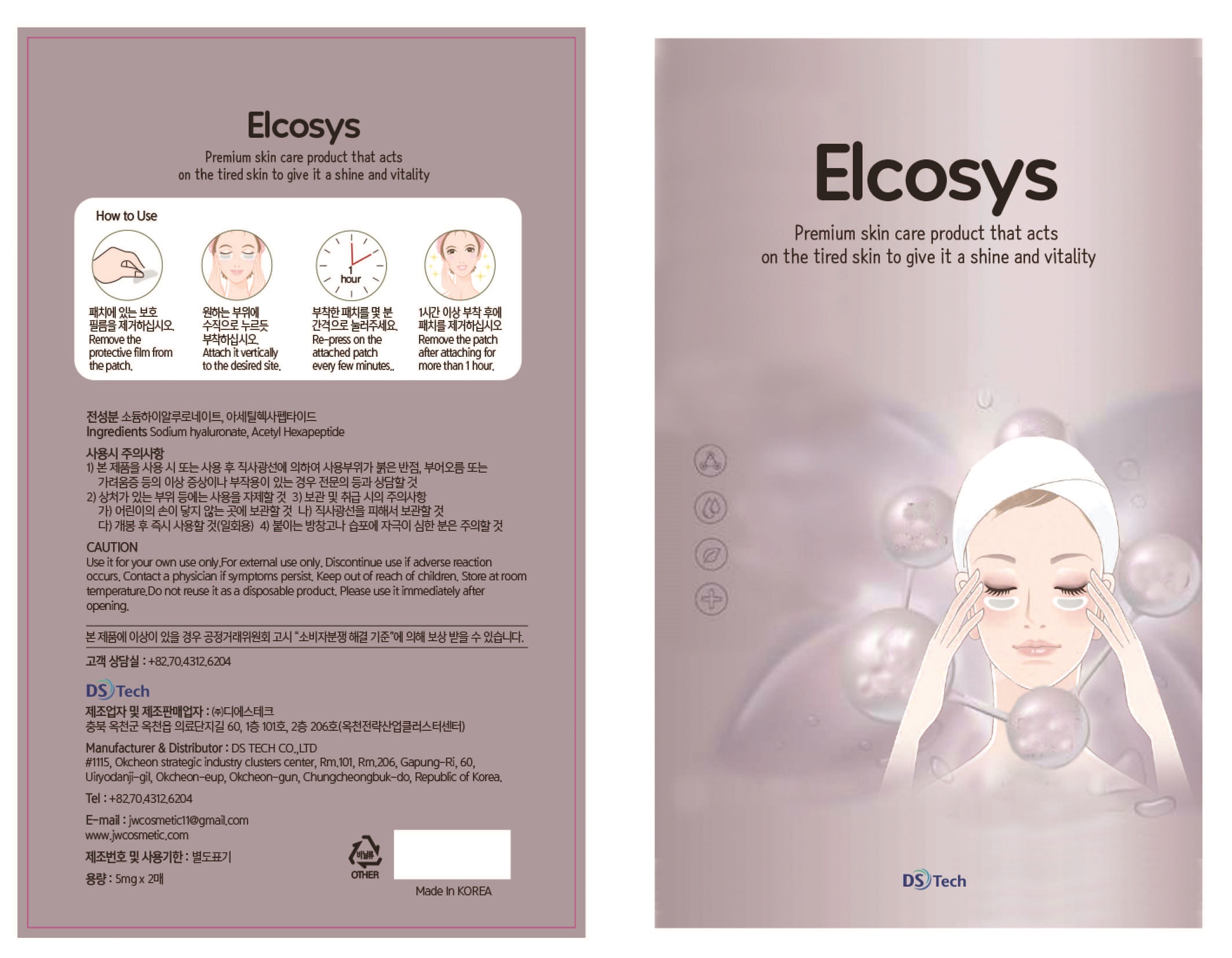 DRUG LABEL: ELCOSYS
NDC: 72910-0001 | Form: PATCH
Manufacturer: DS TECH CO., LTD
Category: otc | Type: HUMAN OTC DRUG LABEL
Date: 20190802

ACTIVE INGREDIENTS: HYALURONATE SODIUM 99.97 mg/100 mg
INACTIVE INGREDIENTS: ACETYL HEXAPEPTIDE-8

Drug Facts

ACTIVE INGREDIENT

Sodium hyaluronate

INACTIVE INGREDIENT

Acetyl Hexapeptide-8

PURPOSE

Premium skin care products that work on tired skin and give shine and vitality

keep out of reach of the children

INDICATIONS AND USAGE

Remove the protective film from the patch.

Attach it vertically to the desired site.

Re-press on thea ttached patch every few minutes..

Remove the patch after attaching for more than 1 hour.

WARNINGS

Use it for your own use only.

For external use only.

Discontinue use if adverse reaction occurs.

Contact a physician if symptoms persist.

Store at room temperature

.Do not reuse it as a disposable product.

Please use it immediately after opening.

DOSAGE AND ADMINISTRATION

for topical use only